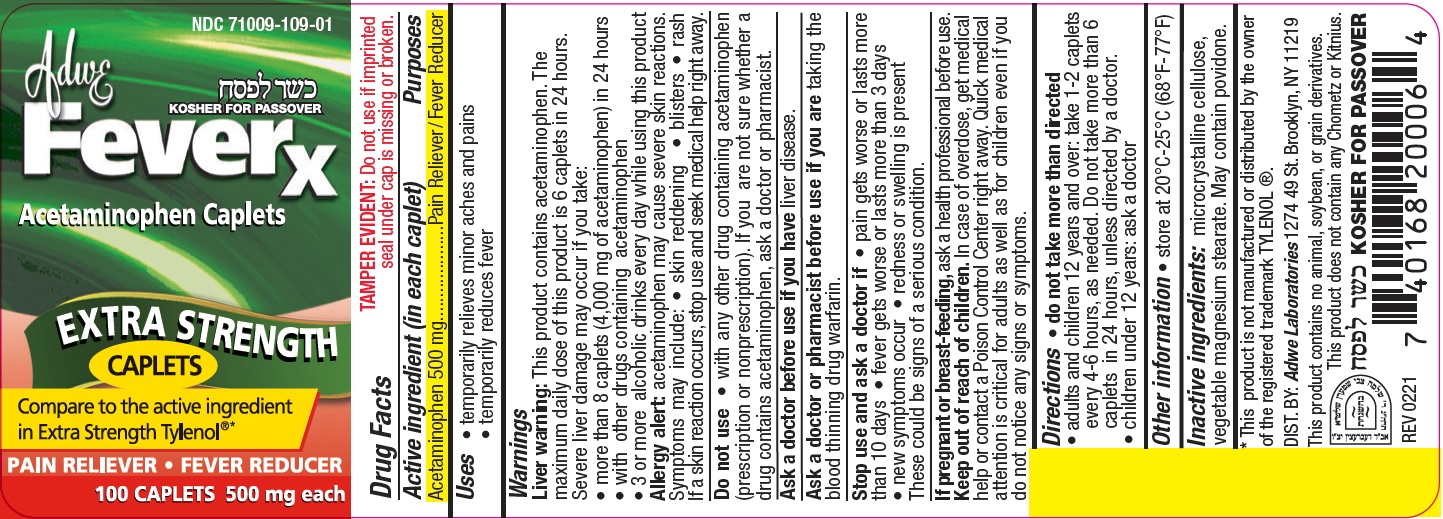 DRUG LABEL: Adwe Feverx Acetaminophen Caplets, 500 mg
NDC: 71009-109 | Form: TABLET
Manufacturer: Aurex Laboratories Limited Liability Company
Category: otc | Type: HUMAN OTC DRUG LABEL
Date: 20250331

ACTIVE INGREDIENTS: ACETAMINOPHEN 500 mg/1 1
INACTIVE INGREDIENTS: MICROCRYSTALLINE CELLULOSE; MAGNESIUM STEARATE; POVIDONE

Adwe Feverx Acetaminophen Caplets, 500 mg

Active Ingredient: Acetaminophen 500 mg

Uses:

- temporarily relives minor aches and pains
- temporarily reduces fever

INDICATIONS AND USAGE

Minor aches and pains, fever.

Warnings

Liver warninig:This product contains acetaminophen. The maximum daily dose of this product is 6 caplets in 24 hours. Severe liver damage may occur if you take:

- more than 8 caplets (4,000 mg of acetaminophen) in 24 hours
- with other drugs containing acetaminophen
- 3 or more alcoholic drinks every day while using this product

Allergy alert:acetaminophen may cause severe skin reactions. Symptoms may include:

- skin reddening
- blisters
- rash

If a skin reaction occurs, stop use and seek medical help right away.

Do not use

- with any other drug containing acetaminophen (prescription or nonprescription). If you are not sure whether a drug contains acetaminophen, ask a doctor or pharmacist.

Ask a doctor before use if you have liver disease.

Ask a doctor or pharmacist before use if you aretaking the blood thinning drug warfarin.

Stop use and ask a doctor if

- pain gets worse or lasts more than 10 days
- fever gets worse or lasts more than 3 days
- new symptoms occur
- redness or swelling is present

These could be signs of a serious condition.

Keep out of reach of children. In case of overdose, get medical help or contact a Poison Control Center right away. Quick medical attention is critical for adults as well as for children even if you do not notice any signs or symptoms.

PREGNANCY OR BREAST FEEDING

If pregnant or breast-feeding,ask a health professional before use.

Directions:

- do not take more than directed
- adults and children 12 years and over: take 1-2 caplets every 4-6 hours, as needed. Do not take more than 6 caplets in 24 hours, unless directed by a doctor.
- children under 12 years: ask a doctor

Other information

- Store at 20° C - 25° C (68° F - 77° F)

Inactive ingredients:

microcrystalline cellulose, vegetable magnesium stearate. May contain povidone.

HOW SUPPLIED

* This product is not manufactured or distributed by the owner of the registered trademark TYLENOL®.

Distributed By:

Adwe Laboratories

1274 49 St. Brooklyn, NY 11219

This product contains no animal, soybean, or grain derivatives.

This product does not contain any Chometx or Krtnius.

REV 0221